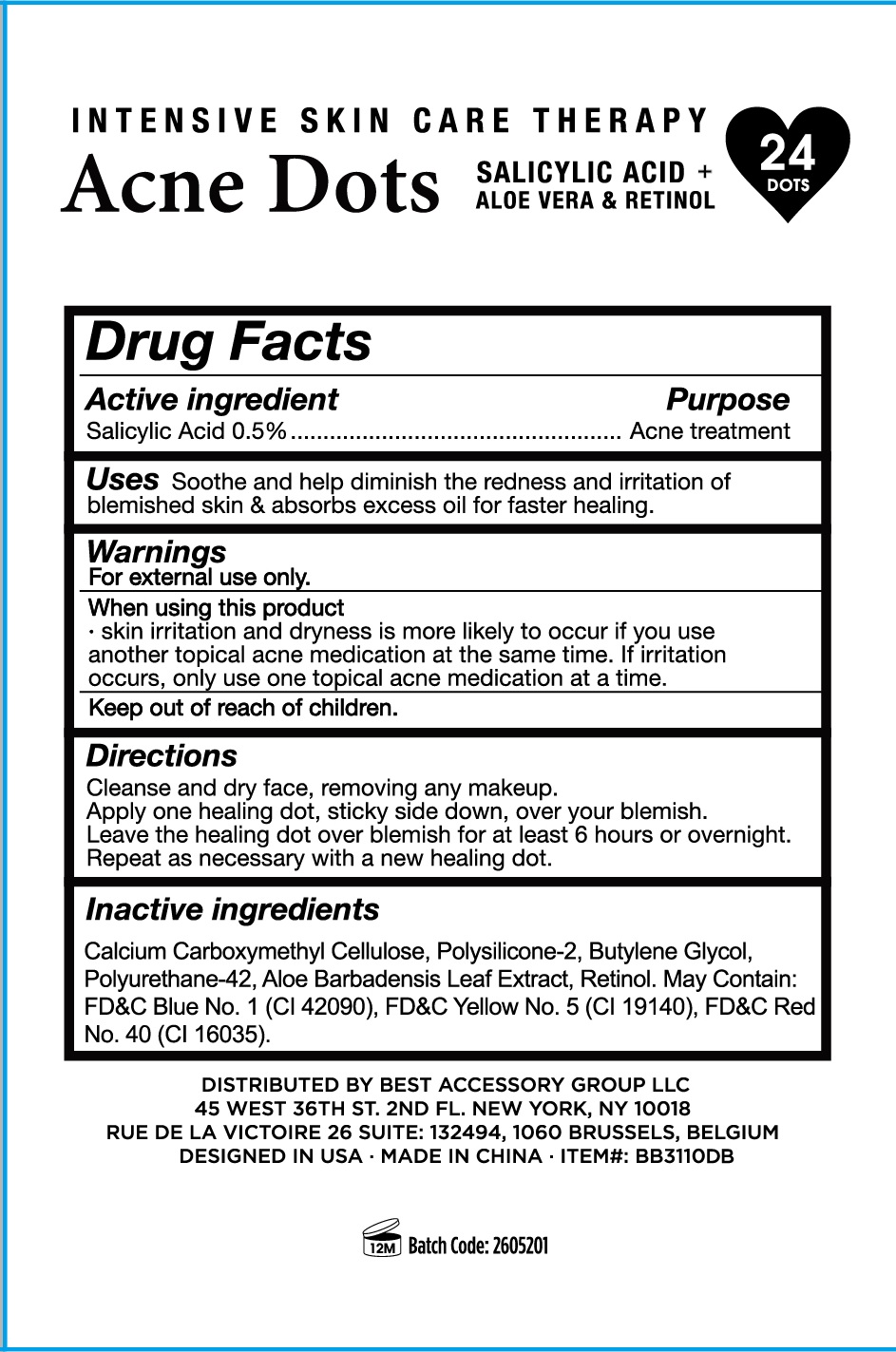 DRUG LABEL: ACNE DOTS (Skin Care Multi-Pack)
NDC: 56136-198 | Form: PATCH
Manufacturer: Ganzhou Olivee Cosmetic Co., Ltd.
Category: otc | Type: HUMAN OTC DRUG LABEL
Date: 20260205

ACTIVE INGREDIENTS: SALICYLIC ACID 0.5 g/100 g
INACTIVE INGREDIENTS: ALOE VERA LEAF; BUTYLENE GLYCOL; FD&C RED NO. 40; FD&C YELLOW NO. 5; FD&C BLUE NO. 1

24 DOTS

Active Ingredients

Salicylic Acid 0.5%

Purpose

Acne Treatment

Uses

soothe and help diminish the redness and irritation of blemished skin and a sorbs excess oil for faster healing.

Directions

- Cleanse and dry facem, removing and makeup.
- Apply one healing dot, sticky side down, over your blemish.
- Leave the healing dot over blemish for at least 6 hours or overnight
- Repeat as necessary with a new healing dot.

Inactive Ingredients

Calcium Carboxymethyl Cellulose, Polysilicone-2, Butylene Glycol. Polyurethane-42, Aloe Barbadensis Leaf Extract. May contain: FD&C Red No. 40 (CI 16035), FD&C Red No.4 (CI 14700), FD&C Yellow No.5 (CI 19140), FD&C Blue No.1 (CI 42090).

Warnings

For external use only.

When using this product

- skin irritation and dryness is more likely to occur if you use another topical acne medication at the same time. If irritation occurs, only use one topical acne medication at a time.

Keep out of reach of children. If swallowed, get medical help or contact a Poison Control center right away